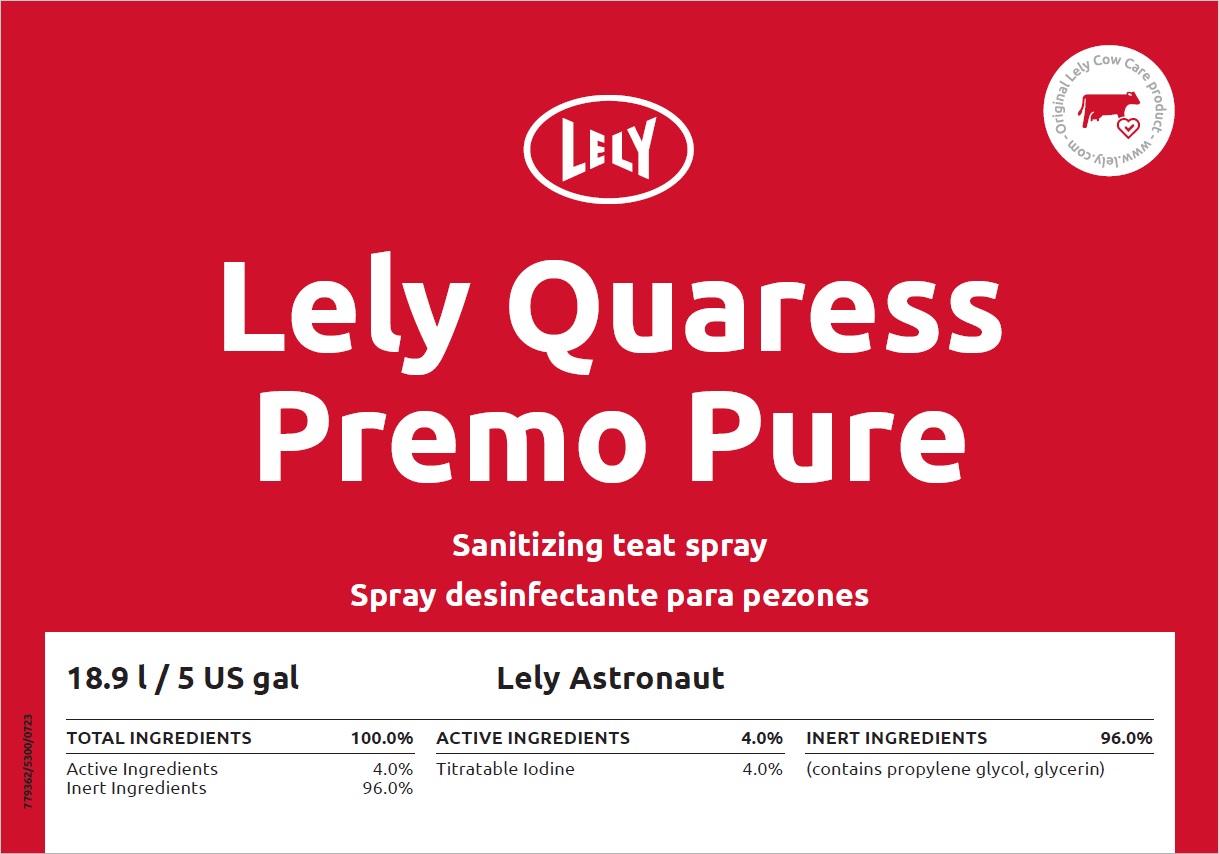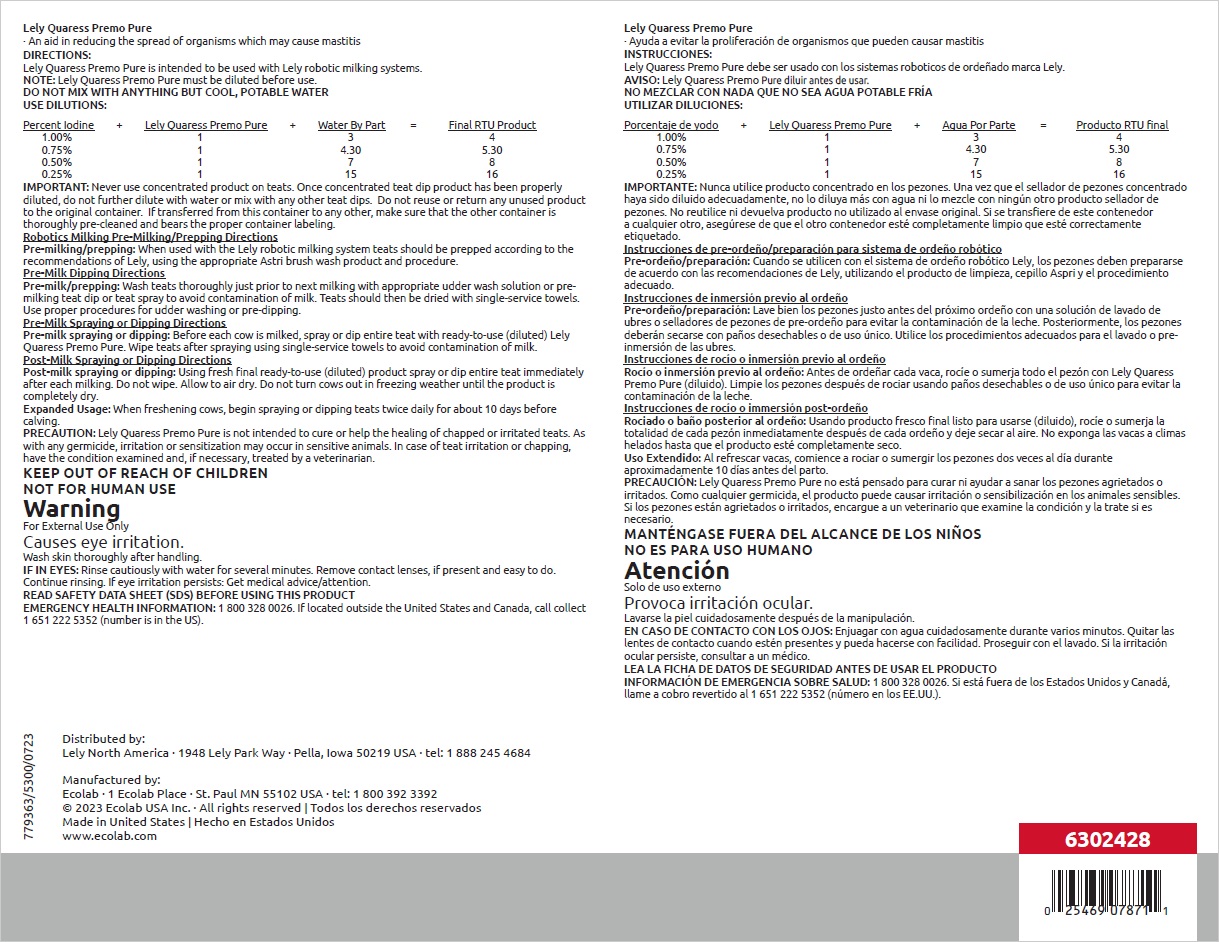 DRUG LABEL: Lely Quaress Premo Pure
NDC: 86190-010 | Form: SOLUTION
Manufacturer: Lely North America, Inc.
Category: animal | Type: OTC ANIMAL DRUG LABEL
Date: 20231030

ACTIVE INGREDIENTS: IODINE 40 mg/1 mL
INACTIVE INGREDIENTS: GLYCERIN; PROPYLENE GLYCOL; WATER

KEEP OUT OF REACH OF CHILDREN

NOT FOR HUMAN USE

Warning

For External Use Only

Causes eye irritation.

Wash skin thoroughly after handling.

IF IN EYES: Rinse cautiously with water for several minutes. Remove contact lenses, if present and easy to do. Continue rinsing. If eye irritation persists: Get medical advice/attention.

OTHER SAFETY INFORMATION

READ SAFETY DATA SHEET (SDS) BEFORE USING THIS PRODUCT

EMERGENCY HEALTH INFORMATION: 1 800 328 0026. If located outside the United States and Canada, call collect 1 651 222 5352 (number is in the US).

Directions:

Lely Quaress Premo Pure is intended to be used with Lely robotic milking systems.

NOTE: Lely Quaress Premo Pure must be diluted before use.

DO NOT MIX WITH ANYTHING BUT COOL, POTABLE WATER

USE DILUTIONS:

Percent Iodine | + | Lely Quaress Premo Pure | + | Water By Part | = | Final RTU Product
1.00% |  | 1 |  | 3 |  | 4
0.75% |  | 1 |  | 4.30 |  | 5.30
0.50% |  | 1 |  | 7 |  | 8
0.25% |  | 1 |  | 15 |  | 16

IMPORTANT: Never use concentrated product on teats. Once concentrated teat dip product has been properly diluted, do not further dilute with water or mix with any other teat dips. Do not reuse or return any unused product to the original container. If transferred from this container to any other, make sure that the other container is thoroughly pre-cleaned and bears the proper container labeling.

Robotics Milking Pre-Milking/Prepping Directions

Pre-milking/prepping: When used with the Lely robotic milking system teats should be prepped according to the recommendations of Lely, using the appropriate Astri brush wash product and procedure.

Pre-Milk Dipping Directions

Pre-milk/prepping: Wash teats thoroughly just prior to next milking with appropriate udder wash solution or pre-milking teat dip or teat spray to avoid contamination of milk. Teats should then be dried with single-service towels. Use proper procedures for udder washing or pre-dipping.

Pre-Milk Spraying or Dipping Directions

Pre-milk spraying or dipping: Before each cow is milked, spray or dip entire teat with ready-to-use (diluted) Lely Quaress Premo Pure. Wipe teats after spraying using single-service towels to avoid contamination of milk.

Post-Milk Spraying or Dipping Directions

Post-milk spraying or dipping: Using fresh final ready-to-use (diluted) product spray or dip entire teat immediately after each milking. Do not wipe. Allow to air dry. Do not turn cows out in freezing weather until the product is completely dry.

Expanded Usage: When freshening cows, begin spraying or dipping teats twice daily for about 10 days before calving.

PRECAUTION: Lely Quaress Premo Pure is not intended to cure or help the healing of chapped or irritated teats. As with any germicide, irritation or sensitization may occur in sensitive animals. In case of teat irritation or chapping, have the condition examined and, if necessary, treated by a veterinarian.

Principal display panel and representative container

Lely Quaress

Premo Pure

Sanitizing teat spray

18.9 l / 5 US gal

Lely Astronaut

TOTAL INGREDIENTS 100.0% | ACTIVE INGREDIENTS 4.0% | INERT INGREDIENTS 96.0%
Active ingredients 4.0% | Titratable Iodine 4.0% | (contains propylene glycol, glycerin)
Inert Ingredients 96.0%

Distributed by:

Lely North America · 1948 Lely Park Way · Pella, Iowa 50219 USA · tel: 1 888 245 4684

Manufactured by:

Ecolab · 1 Ecolab Place · St. Paul MN 55102 USA · tel: 1 800 392 3392

© 2023 Ecolab USA Inc. · All rights reserved | Todos los derechos reservados

Made in United States | Hecho en Estados Unidos

www.ecolab.com